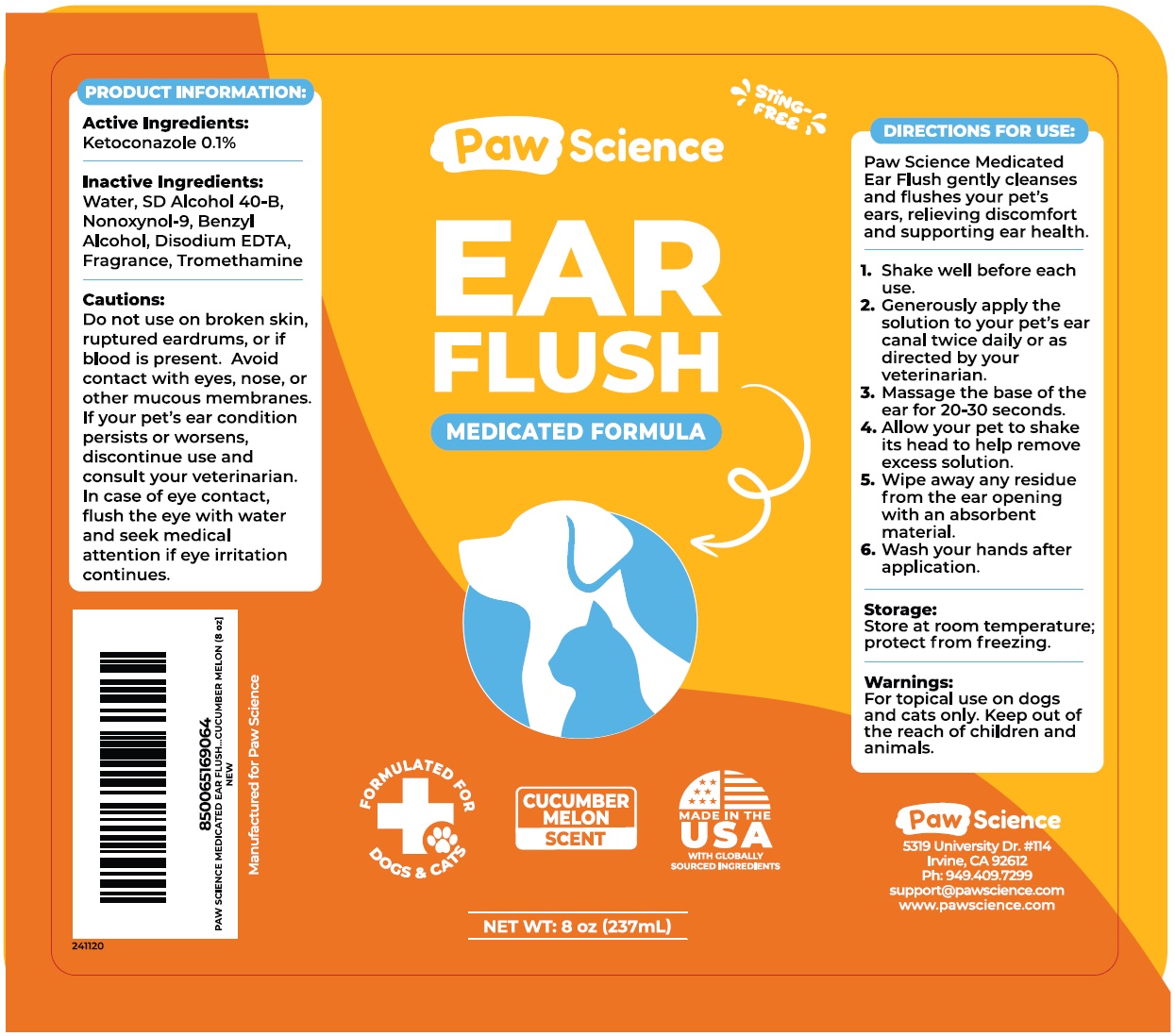 DRUG LABEL: Paw Science MEDICATED EAR FLUSH
NDC: 86207-002 | Form: SOLUTION
Manufacturer: Pet Science LLC
Category: animal | Type: OTC ANIMAL DRUG LABEL
Date: 20241204

ACTIVE INGREDIENTS: KETOCONAZOLE 1 mg/1 mL
INACTIVE INGREDIENTS: WATER; ALCOHOL; NONOXYNOL-9; BENZYL ALCOHOL; EDETATE DISODIUM; TROMETHAMINE

Paw Science MEDICATED EAR FLUSH

Active Ingredients:

Ketoconazole 0.1%

Inactive Ingredients:

Water, SD Alcohol 40-B, Nonoxynol-9, Benzyl Alcohol, Disodium EDTA, Fragrance, Tromethamine

Cautions:

Do not use on broken skin, ruptured eardrums, or if blood is present. Avoid contact with eyes, nose, or other mucous membranes. If your pet’s ear condition persists or worsens, discontinue use and consult your veterinarian. In case of eye contact, flush the eye with water and seek medical attention if eye irritation continues.

DIRECTIONS FOR USE:

Paw Science Medicated Ear Flush gently cleanses and flushes your pet’s ears, relieving discomfort and supporting ear health.

1. Shake well before each use.
2. Generously apply the solution to your pet’s ear canal twice daily or as directed by your veterinarian.
3. Massage the base of the ear for 20-30 seconds.
4. Allow your pet to shake its head to help remove excess solution.
5. Wipe away any residue from the ear opening with an absorbent material.
6. Wash your hands after application.

Storage:

Store at room temperature; protect from freezing.

Warnings:

For topical use on dogs and cats only. Keep out of the reach of children and animals.

STING-FREE

MEDICATED FORMULA

FORMULATED FOR DOGS & CATS

CUCUMBER MELON SCENT

MADE IN THE USA WITH GLOBALLY SOURCED INGREDIENTS

Paw Science
5319 University Dr. #114 Irvine, CA 92612 Ph: 949.409.7299 support@pawscience.comwww.pawscience.com

Manufactured for Paw Science